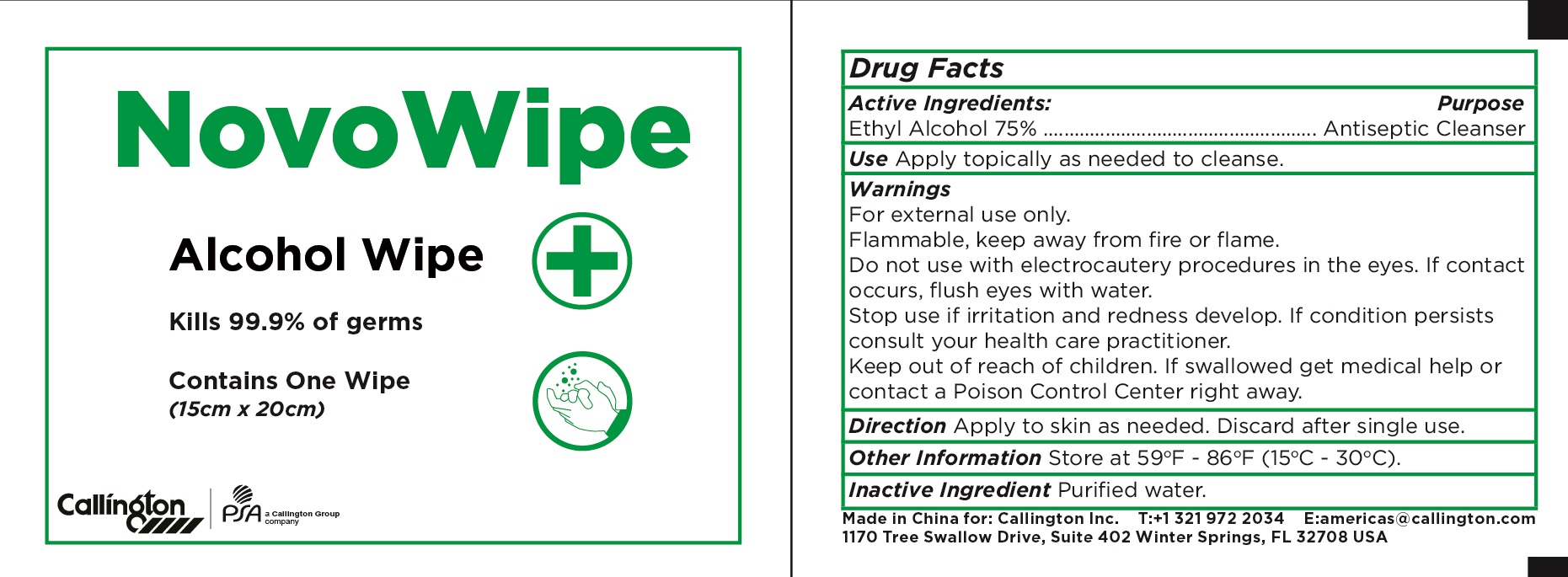 DRUG LABEL: Novo wipe
NDC: 71734-262 | Form: SWAB
Manufacturer: JIANGMEN SHUIZIRUN SANITARY ARTICLES CO., LTD.
Category: otc | Type: HUMAN OTC DRUG LABEL
Date: 20250512

ACTIVE INGREDIENTS: ALCOHOL 75 g/100 g
INACTIVE INGREDIENTS: WATER

DRUG FACTS

Active Ingredient

Ethyl Alcohol ................. 75%

Purpose

Antiseptic Clanser

Uses:

Apply topically as needed to cleanse.

Warnings

For external use only.

Flammable, keep away from fire or flame.

Do not use with electrocautery procedurs in the eyes. If contact occurs, flush eyes with water.

Stop use if irritation develops. If condition persists consult your health car practitioner.

Other Information:

Store at 59℉-86℉ (15℃-30℃).

Keep out of reach of children.

if swallowed get medical help or contact a Poison Control Center right away.

Directions

Apply to skin as needed. Discard after single use.

Inactive Ingredients:

Purified Water